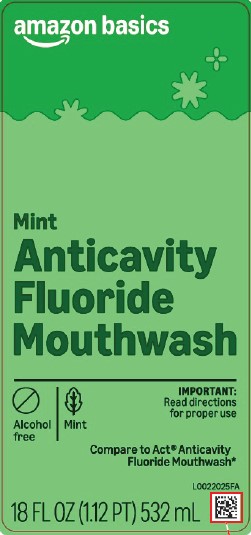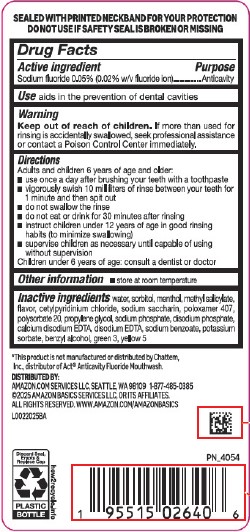 DRUG LABEL: Anticavity Fluoride Rinse
NDC: 72288-213 | Form: MOUTHWASH
Manufacturer: Amazon.com Services LLC
Category: otc | Type: HUMAN OTC DRUG LABEL
Date: 20250915

ACTIVE INGREDIENTS: SODIUM FLUORIDE 0.2 mg/1 mL
INACTIVE INGREDIENTS: WATER; SORBITOL; MENTHOL; METHYL SALICYLATE; CETYLPYRIDINIUM CHLORIDE; SACCHARIN SODIUM; POLOXAMER 407; POLYSORBATE 20; PROPYLENE GLYCOL; SODIUM PHOSPHATE; SODIUM PHOSPHATE, DIBASIC, ANHYDROUS; EDETATE CALCIUM DISODIUM ANHYDROUS; EDETATE DISODIUM ANHYDROUS; SODIUM BENZOATE; POTASSIUM SORBATE; BENZYL ALCOHOL; FD&C GREEN NO. 3; FD&C YELLOW NO. 5

Basics 213.002/213AE rev 2
Anticavity Fluoride Rinse, Mint

Tamper Evident Statement

SEALED WITH PRINTED NECKBAND FOR YOUR PROTECTION

DO NOT USE IF SAFETY SEAL IS BROKEN OR MISSING

Active ingredient

Sodium fluoride 0.05% (0.02% w/v fluoride ion)

Purpose

Anticavity

Use

aids in the prevention of dental cavities

Warning

for this product

Keep out of reach of children.

If more than used for rinsing is accidentally swallowed, seek professional assistance or contact a Poison Control Center immediately.

Directiions

Adults and children 6 years of age and older:

- use once a day after brushing your teeth with a toothpaste
- vigorously swish 10 milliliters of rinse between your teeth for 1 minute and then spit out
- do not swallow the rinse
- do not eat or drink for 30 minutes after rinsing
- instruct children under 12 years of age in good rinsing habits (to minimize swallowing)
- supervise children as necessary until capable of using without supervision

Children under 6 years of age: consult a dentist or doctor

Other information

- store at room temperature

Inactive ingredients

water, sorbitol, menthol, methyl salicylate, flavor, cetylpyridinium chloride, sodium saccharin, poloxamer 407, polysorbate 20, propylene glycol, sodium phosphate, disodium phosphate, calcium disodium EDTA, disodium EDTA, sodium benzoate, potassium sorbate, benzyl alcohol, green 3, yellow 5

Disclaimer

*This product is not manufactured or distributed by Chattem, Inc., distributor of ActAnticavity Flouride Mouthwash.

Adverse reactions

DISTRIBUTED BY:

Amazon.com Services, LLC, Seattle, WA 98109 1-877-485-0385

©2025 Amazon Basics Services LLC or its affiliates.

All rights reserved. www.amazon.com/amazonbasics

Discard Seal, Empty & Replace Cap

PLASTIC BOTTLE

how2recycle.info

Principal display panel

amazon basics

Mint

Anticavity

Fluoride

Mouthwash

Alcohol Free

Mint

IMPORTANT: READ DIRECTIONS FOR PROPER USE

Compare to Act® Anticavity Fluoride Mouthwash*

18 FL OZ (1.12 PT) 532 mL